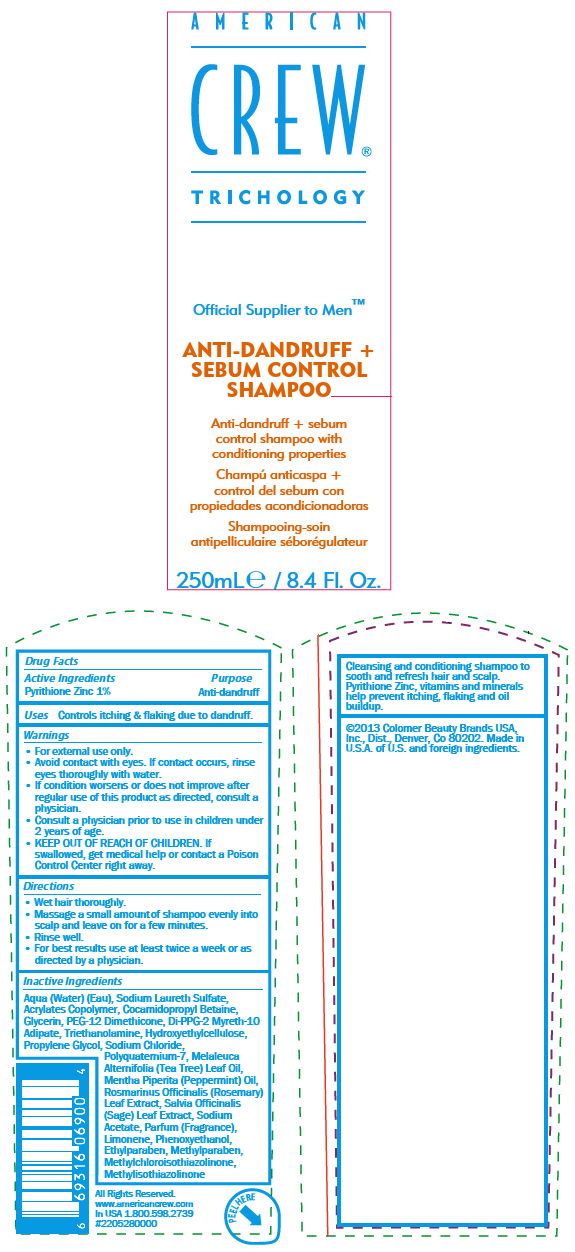 DRUG LABEL: American Crew Anti-Dandruff plus Sebum Control
NDC: 42743-4700 | Form: SHAMPOO
Manufacturer: Colomer USA, Ltd.
Category: otc | Type: HUMAN OTC DRUG LABEL
Date: 20140611

ACTIVE INGREDIENTS: Pyrithione Zinc 10 mg/1 mL
INACTIVE INGREDIENTS: SODIUM LAURETH-3 SULFATE; COCAMIDOPROPYL BETAINE; GLYCERIN; PEG-12 DIMETHICONE (300 CST); DI-PPG-2 MYRETH-10 ADIPATE; TROLAMINE; HYDROXYETHYL CELLULOSE (100 MPA.S AT 2%); PROPYLENE GLYCOL; SODIUM CHLORIDE; POLYQUATERNIUM-7 (70/30 ACRYLAMIDE/DADMAC; 1600000 MW); TEA TREE OIL; PEPPERMINT OIL; ROSEMARY; SAGE; SODIUM ACETATE; LIMONENE, (+)-; PHENOXYETHANOL; ETHYLPARABEN; METHYLPARABEN; METHYLCHLOROISOTHIAZOLINONE; METHYLISOTHIAZOLINONE

American Crew® Anti-Dandruff + Sebum Control Shampoo

Drug Facts

Active Ingredients

Pyrithione Zinc 1%

Purpose

Anti-dandruff

Uses

Controls itching & flaking due to dandruff.

Warnings

- For external use only.
- Avoid contact with eyes. If contact occurs, rinse eyes thoroughly with water.

ASK DOCTOR

- If condition worsens or does not improve after regular use of this product as directed, consult a physician.
- Consult a physician prior to use in children under 2 years of age.

- KEEP OUT OF REACH OF CHILDREN. If swallowed, get medical help or contact a Poison Control Center right away.

Directions

- Wet hair thoroughly.
- Massage a small amount of shampoo evenly into scalp and leave on for a few minutes.
- Rinse well.
- For best results use at least twice a week or as directed by a physician.

Inactive Ingredients

Aqua (Water) (Eau), Sodium Laureth Sulfate, Acrylates Copolymer, Cocamidopropyl Betaine, Glycerin, PEG-12 Dimethicone, Di-PPG-2 Myreth-10 Adipate, Triethanolamine, Hydroxyethylcellulose, Propylene Glycol, Sodium Chloride, Polyquaternium-7, Melaleuca Alternifolia (Tea Tree) Leaf Oil, Mentha Piperita (Peppermint) Oil, Rosmarinus Officinalis (Rosemary) Leaf Extract, Salvia Officinalis (Sage) Leaf Extract, Sodium Acetate, Parfum (Fragrance), Limonene, Phenoxyethanol, Ethylparaben, Methylparaben, Methylchloroisothiazolinone, Methylisothiazolinone

PRINCIPAL DISPLAY PANEL - 250mL Bottle Label

AMERICAN
CREW®
TRICHOLOLGY

Official Supplier to Men™

ANTI-DANDRUFF +
SEBUM CONTROL
SHAMPOO

Anti-dandruff + sebum
control shampoo with
conditioning properties

250mL e / 8.4 Fl. Oz.